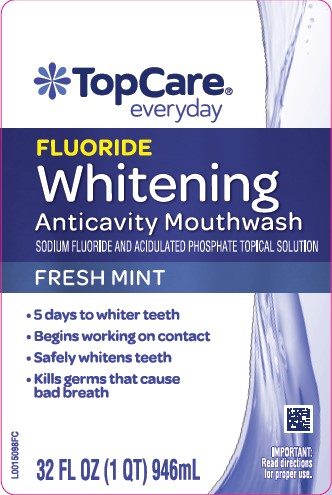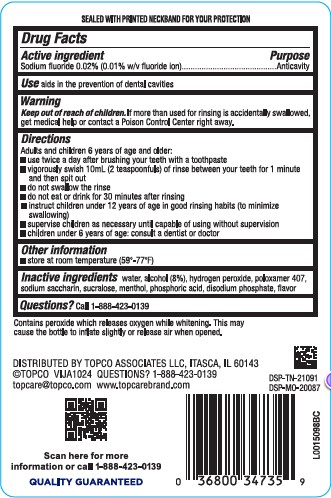 DRUG LABEL: Anticavity
NDC: 36800-803 | Form: MOUTHWASH
Manufacturer: Topco Associates LLC
Category: otc | Type: HUMAN OTC DRUG LABEL
Date: 20260213

ACTIVE INGREDIENTS: SODIUM FLUORIDE 0.1 mg/1 mL
INACTIVE INGREDIENTS: WATER; ALCOHOL; HYDROGEN PEROXIDE; POLOXAMER 407; SACCHARIN SODIUM; SUCRALOSE; MENTHOL; PHOSPHORIC ACID; SODIUM PHOSPHATE, DIBASIC, ANHYDROUS

Top Care 435.000/435AA
Glowing White Anticavity Mouthrinse

Tamper Evident Statement

SEALED WITH PRINTED NECKBAND FOR YOUR PROTECTION

Active Ingredient

Sodium fluoride 0.02% (0.01% w/v fluoride ion)

Purpose

Anticavity

Use

aids in the prevention of dental cavities

Warnings

for this product

Keep out of reach of children.

If more than used for rinsing is accidentally swallowed, get medical help or contact a Poison Control Center right away.

Directions

Adults and children 6 years of age and older:

- use twice a day after brushing your teeth with a toothpaste
- vigorously swish 10 mL (2 teaspoonfuls) of rinse between your teeth for 1 minute and then spit out
- do not swallow the rinse
- do not eat or drink for 30 minutes after rinsing
- instruct children under 12 years of age in good rinsing habits (to minimize swallowing)
- supervise children as necessary until capable of using without supervision
- children under 6 years of age: consult a dentist or doctor

Other information

- store at room temperature (59º-77ºF)

Inactive ingredients

water, alcohol (8%), hydrogen peroxide, poloxamer 407, sodium saccharin, sucralose, menthol, phosphoric acid, disodium phosphate, flavor

Questions?

Call 1-888-423-0139

other information

Contains peroxide which releases oxygen while whitening. This may cause the bottle to inflate slightly or release air when opened.

Adverse reactions

DISTRIBUTED BY TOPCO ASSOCIATES LLC, ITASCA, IL 60143

©TOPCO VIJA1024 QUESTIONS? 1-888-423-0139

topcare@topco.com www.topcarebrand.com

DSP-TN-21091

DSP-MO-20087

Scan here for more information or call 1-888-423-0139

QUALITY GUARANTEED

principal display panel

Top Care®

everyday

FLUORIDE

Whitening

Antivavity Mouthwash

SODIUM FLUORIDE AND ACIDULATED PHOSPHATE TOPICAL SOLUTION

FRESH MINT

- 5 days to whiter teeth
- Begins working on contact
- Safely whitens teeth
- Kills germs that cause bad breath

IMPORTANT: Read direction for proper use.

32 FL OZ (1 QT) 946 mL